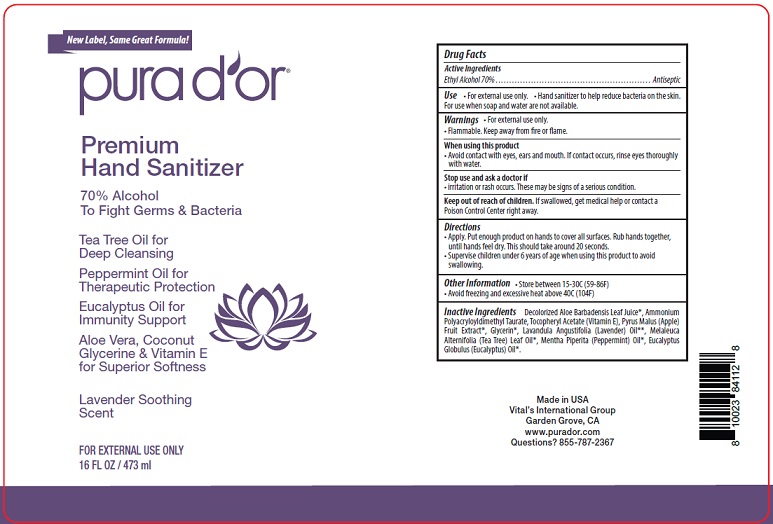 DRUG LABEL: Purador
NDC: 69019-002 | Form: GEL
Manufacturer: Vitals Cosmetics International
Category: otc | Type: HUMAN OTC DRUG LABEL
Date: 20220331

ACTIVE INGREDIENTS: ALCOHOL 70 mL/100 mL
INACTIVE INGREDIENTS: ALOE VERA LEAF; AMMONIUM POLYACRYLOYLDIMETHYL TAURATE (55000 MPA.S); .ALPHA.-TOCOPHEROL ACETATE; APPLE; GLYCERIN; WEST INDIAN LEMONGRASS OIL; TEA LEAF OIL; PEPPERMINT OIL; LAVENDER OIL; EUCALYPTUS OIL

Active Ingredient

Ethyl Alcohol 70% v/v.

Purpose

Antiseptic

Use

- Hand Sanitizer to help reduce bacteria on the skin.
- For use when soap and water are not available.

Warnings

For external use only.

Flammable. Keep away from heat or flame

When using this product Avoid contact with eyes, ears and mouth. If contact occurs, rinse eyes thoroughly with water.

Stop use and ask a doctor if irritation or rash occurs. These may be signs of a serious condition.

Keep out of reach of children. If swallowed, get medical help or contact a Poison Control Center right away.

Directions

- Apply. Put enough product on hands to cover all surfaces. Rub hands together until feel dry. This should take around 20 seconds.
- Supervise children under 6 years of age when using this product to avoid swallowing.

Other information

- Store between 15-30^0C (59-86^0F)
- Avoid freezing and excessive heat above 40^0C (104^0F)

Inactive ingredients

Decolorized Aloe Barbadensis Leaf Juice*, Ammonium Polyacryloyldimethyl Taurate, Tocopheryl Acetate (Vitamin E), Pyrus Malus (Apple)
Fruit Extract*, Glycerin*, Lavandula Angustifolia (Lavender) Oil**, Melaleuca Alternifolia (Tea Tree) Leaf Oil*, Mentha Piperita (Peppermint) Oil*, Eucalyptus Globulus (Eucalyptus) Oil*.